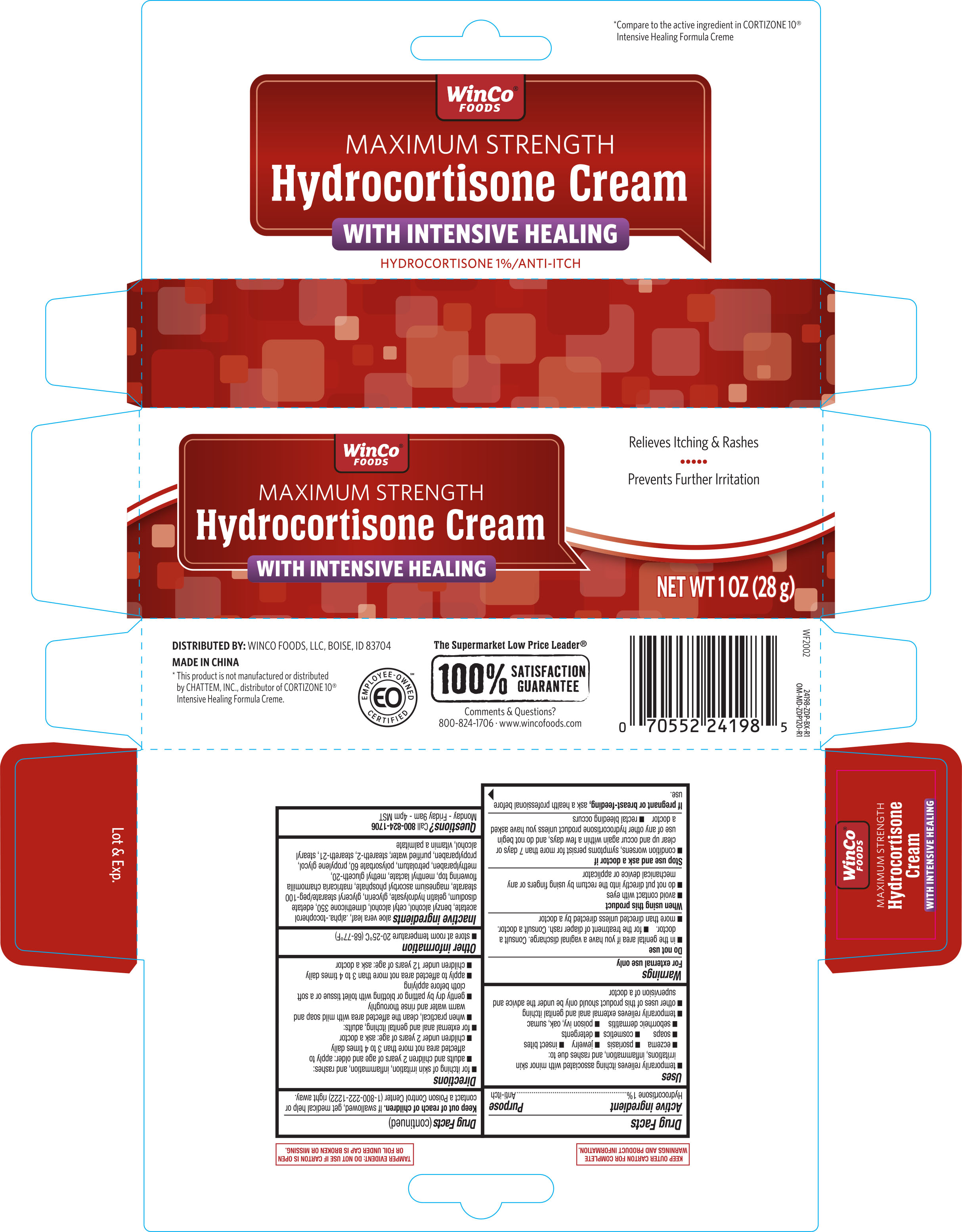 DRUG LABEL: WinCo Foods Hydrocortisone Cream Intensive Healing
NDC: 67091-419 | Form: CREAM
Manufacturer: WINCO FOODS, LLC
Category: otc | Type: HUMAN OTC DRUG LABEL
Date: 20251022

ACTIVE INGREDIENTS: HYDROCORTISONE 10 mg/1 g
INACTIVE INGREDIENTS: MENTHYL LACTATE, (-)-; METHYLPARABEN; POLYSORBATE 60; PROPYLENE GLYCOL; PROPYLPARABEN; DIMETHICONE 350; GLYCERYL STEARATE/PEG-100 STEARATE; MAGNESIUM ASCORBYL PHOSPHATE; MATRICARIA CHAMOMILLA FLOWERING TOP; PETROLATUM; WATER; ALOE VERA LEAF; STEARETH-2; VITAMIN A PALMITATE; STEARYL ALCOHOL; GLYCERIN; METHYL GLUCETH-20; STEARETH-21; CETYL ALCOHOL; EDETATE DISODIUM; GELATIN HYDROLYSATE (PORCINE SKIN, MW 3000); .ALPHA.-TOCOPHEROL ACETATE; BENZYL ALCOHOL

Winco Hydrocortisone Cream Intensive Healing 1oz 24198 ZDP

Active ingredient........................................................................Purpose

Hydrocortisone 1%........................................................................Anti-itch

Uses

temporarily relieves itching associated with minor skin irritations, inflammation, and rashes due to:

- eczema
- psoriasis
- jewelry
- insect bites
- soaps
- cosmetics
- detergents
- seborrheic dermatitis
- poison ivy, oak, sumac

temporarily relieves external anal and genital itching

other uses of this product should only be under the advice and supervision of a doctor

Warnings

For external use only

Do not use

- in the genital area if you have a vaginal discharge. Consult a doctor.
- for the treatment of diaper rash. Consult a doctor.
- more than directed unless directed by a doctor

When using this product

- avoid contact with eyes
- do not put directly into the rectum by using finger or any mechanical device or applicator

Stop use and ask a doctor if

- condition worsens, symptoms persist for more than 7 days or clear up and occur again within a few days, and do not begin use of any other hydrocortisone product unless you have asked a doctor
- rectal bleeding occurs

PREGNANCY OR BREAST FEEDING

If pregnant or breast-feeding,ask a health professional before use.

Keep out of reach of children.If swallowed, get medical help or contact a Poison Control Center (1-800-222-1222) right away.

Directions

for itching of skin irritation, inflammation, and rashes:

- adults and children 2 years of age and older: apply to affected area not more than 3 to 4 times daily
- children under 2 years of age: ask a doctor

for external anal and genital itching, adults:

- when practical, clean the affected area with mild soap and warm water and rinse thoroughly
- gently dry by patting or blotting with toilet tissue or a soft cloth before applying
- apply to affected area not more than 3 to 4 times daily
- children under 12 years of age: ask a doctor

Other information

- store at room temperature 20-25ºC (68-77ºF)

INACTIVE INGREDIENT

Inactive ingredientsaloe vera leaf, .alpha.-tocopherol acetate, benzyl alcohol, cetyl alcohol, dimethicone 350, edetate disodium, gelatin hydrolysate, glycerin, glyceryl stearate/peg-100 stearate, magnesium ascorbyl phosphate, matricaria chamomilla flowering top, menthyl lactate, methyl gluceth-20, methylparaben, petrolatum, polysorbate 60, propylene glycol, propylparaben, purified water, steareth-2, steareth-21, stearyl alcohol, vitamin a palmitate

DOSAGE AND ADMINISTRATION

DISTRIBUTED BY:

WINCO FOODS, LLC,

BOISE, ID 83704

MADE IN CHINA